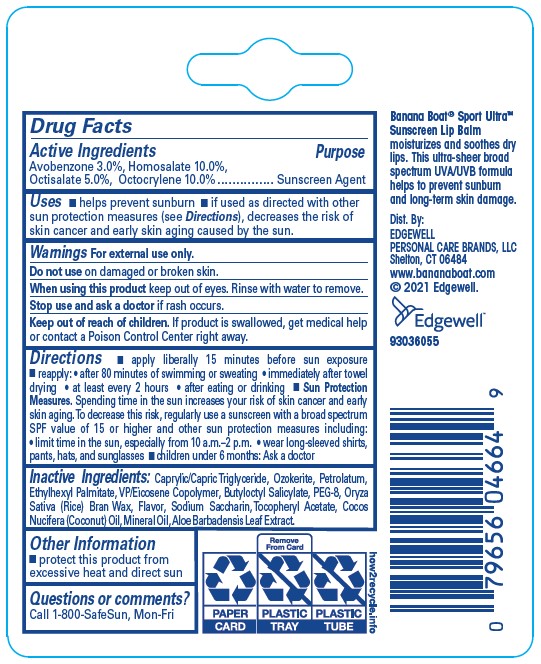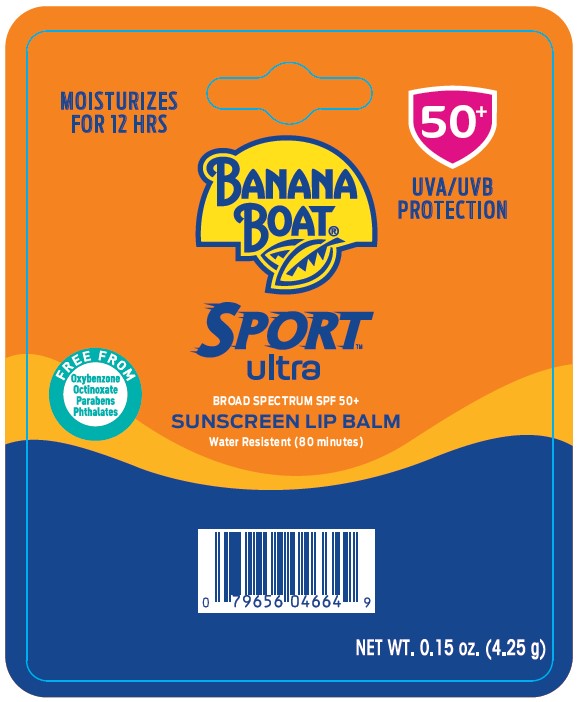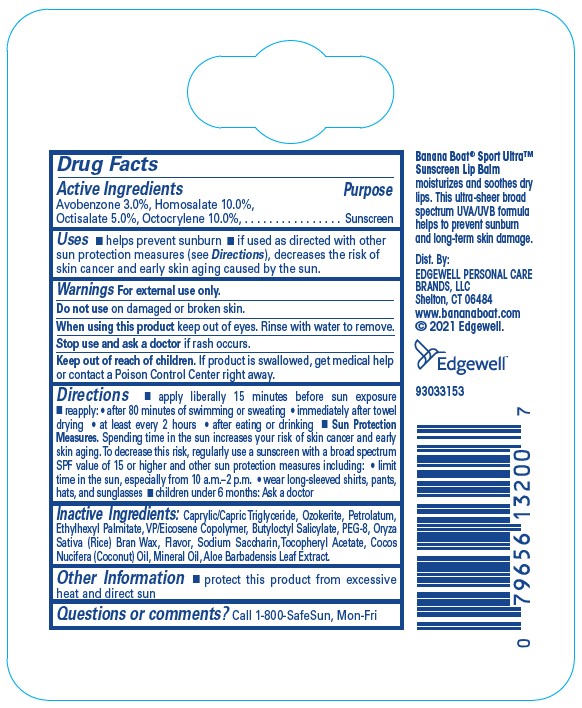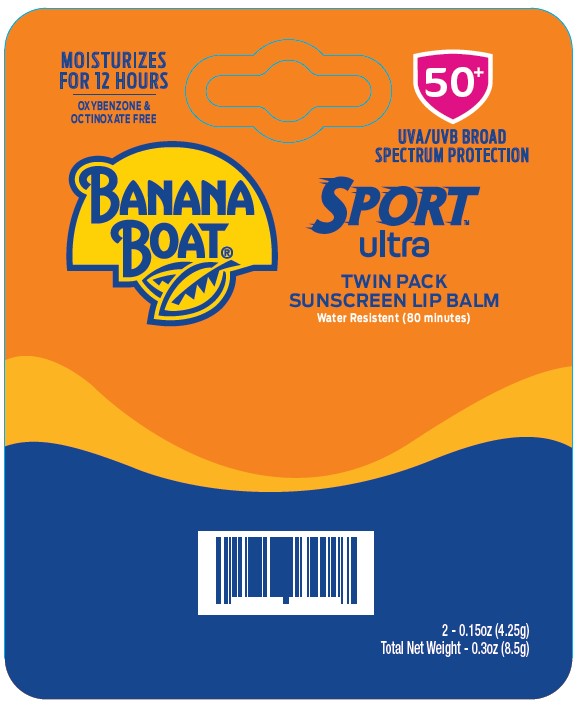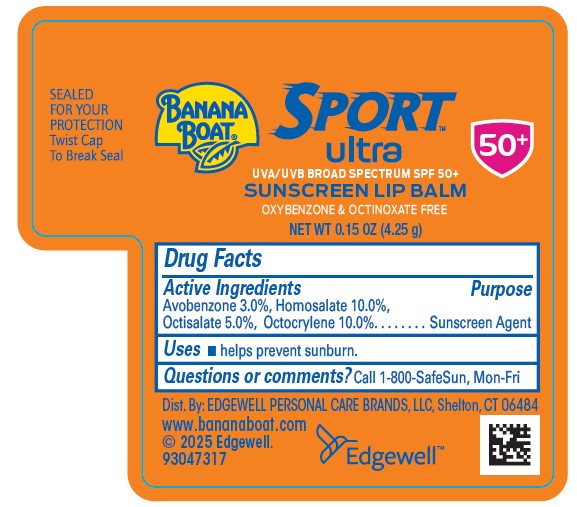 DRUG LABEL: Banana Boat Sport Ultra Broad Spectrum SPF 50 Plus Sunscreen Lip Balm
NDC: 63354-597 | Form: STICK
Manufacturer: Edgewell Personal Care Brands LLC
Category: otc | Type: HUMAN OTC DRUG LABEL
Date: 20251204

ACTIVE INGREDIENTS: AVOBENZONE 3 g/100 g; OCTOCRYLENE 10 g/100 g; HOMOSALATE 10 g/100 g; OCTISALATE 5 g/100 g
INACTIVE INGREDIENTS: CERESIN; ETHYLHEXYL PALMITATE; SACCHARIN SODIUM ANHYDROUS; .ALPHA.-TOCOPHEROL ACETATE; COCONUT OIL; MINERAL OIL; POLYETHYLENE GLYCOL 400; ALOE VERA LEAF; PETROLATUM; RICE BRAN; BUTYLOCTYL SALICYLATE; MEDIUM-CHAIN TRIGLYCERIDES; VINYLPYRROLIDONE/EICOSENE COPOLYMER

Active Ingredients

Avobenzone 3.0%, Homosalate 10.0%, Octisalate 5.0%, Octocrylene 10.0%

Purpose

Sunscreen Agent

Uses

• helps prevent sunburn • if used as directed with other sun protection measures (see Directions), decreases the risk of skin cancer and early skin aging caused by the sun.

Warnings

For external use only.

Do not use

on damaged or broken skin.

When using this product

keep out of eyes. Rinse with water to remove.

Stop use and ask a doctor

if rash occurs.

Keep out of reach of children.

If product is swallowed, get medical help or contact a Poison Control Center right away.

Directions

• apply liberally 15 minutes before sun exposure • reapply: • after 80 minutes of swimming or sweating • immediately after towel drying • at least every 2 hours • after eating or drinking • Sun Protection Measures. Spending time in the sun increases your risk of skin cancer and early skin aging. To decrease this risk, regularly use a sunscreen with a broad spectrum SPF value of 15 or higher and other sun protection measures including: • limit time in the sun, especially from 10 a.m.–2 p.m. • wear long-sleeved shirts, pants, hats, and sunglasses • children under 6 months: Ask a doctor

Inactive Ingredients

Caprylic/Capric Triglyceride, Ozokerite, Petrolatum, Ethylhexyl Palmitate, VP/Eicosene Copolymer, Butyloctyl Salicylate, PEG-8, Oryza Sativa (Rice) Bran Wax, Flavor, Sodium Saccharin, Tocopheryl Acetate, Cocos Nucifera (Coconut) Oil, Mineral Oil, Aloe Barbadensis Leaf Extract.

Other Information

protect this product from excessive heat and direct sun

Questions or comments?

Call 1-800-SafeSun, Mon-Fri

Principal Display Panel

MOISURIZES
FOR 12 HRS
50+
UVA/UVB
PROTECTION
BANANA
BOAT(R)
SPORT
ultra
BROAD SPECTRUM SPF 50+
SUNSCREEN LIP BALM
Water Resistant (80 minutes)
FREE FROM
Oxybenzone
Octinoxate
Parabens
Phthalates
NET WT. 0.15 oz. (4.25 g)

MOISURIZES
FOR 12 HRS
OXYBENZONE &
OCTINOXATE FREE
50+
UVA/UVB BROAD
SPECTRUM PROTECTION
BANANA
BOAT(R)
SPORT
ultra
TWIN PACK
SUNSCREEN LIP BALM
Water Resistant (80 minutes)
2 - 0.15oz (4.25g)
Total Net Weight - 0.3oz (8.5g)